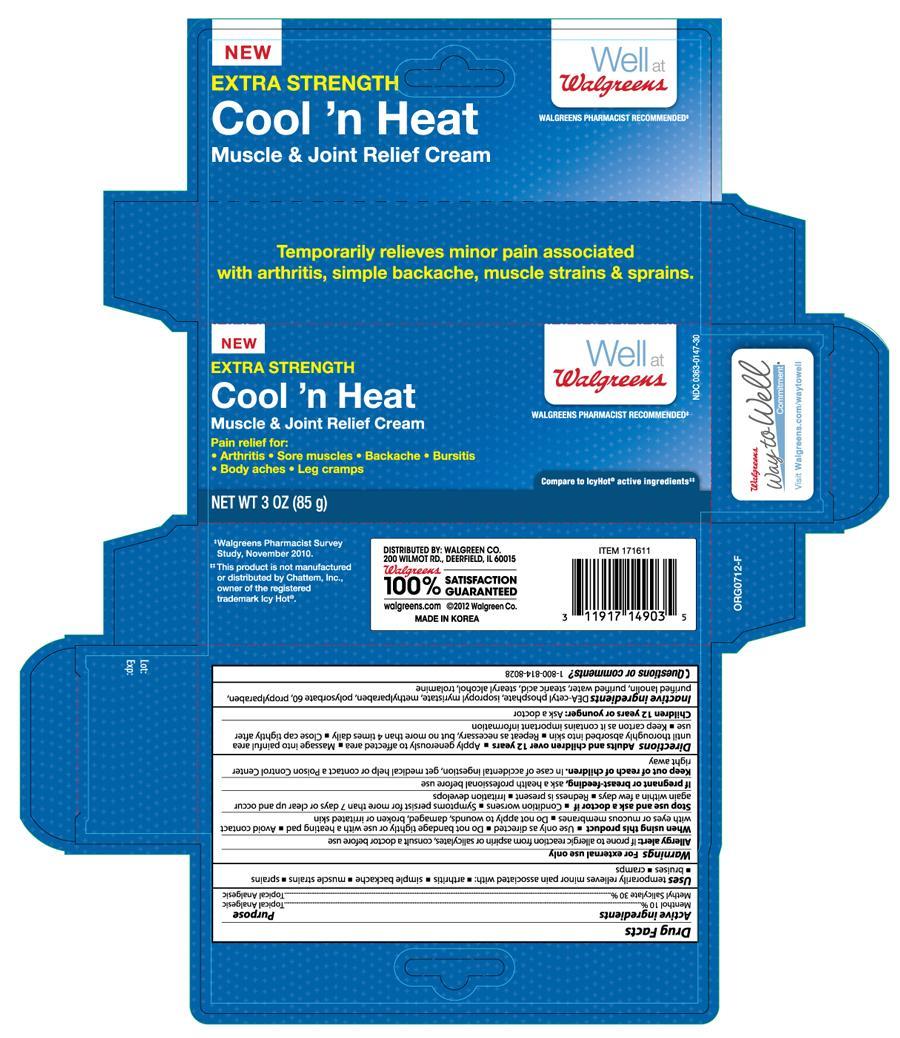 DRUG LABEL: WALGREENS COOL AND HEAT MUSCLE AND JOINT RELIEF
                
NDC: 0363-0147 | Form: CREAM
Manufacturer: WALGREEN COMPANY
Category: otc | Type: HUMAN OTC DRUG LABEL
Date: 20130331

ACTIVE INGREDIENTS: MENTHOL 10 g/100 g; METHYL SALICYLATE 30 g/100 g
INACTIVE INGREDIENTS: CETYL ESTERS WAX; OLETH-3 PHOSPHATE; STEARIC ACID; TROLAMINE; WATER

Drug Facts

Active ingredients Purpose

Menthol 10%............................................................Topical Analgesic

Methyl Salicylate 30%...............................................Topical Analgesic

PURPOSE

Uses temporarily relieves minor pain associated with:

- arthritis
- simple backache
- muscle strains
- sprains
- bruises
- cramps

Warnings For external use only

Allergy alert: If prone to allergic reaction from aspirin or salicylates, consult a doctor before use

When using this product

- Use only as directed
- Do not bandage tightly or use with a heating pad
- Avoid contact with eyes or mucous membranes
- Do not apply to wounds, damaged, broken or irritated skin

Stop use and ask a doctor if

- Condition worsens
- Symptoms persist for more than 7 days or clear up and occur again within a few days
- Redness is present
- Irritation develops

PREGNANCY OR BREAST FEEDING

If pregnant or breast-feeding, ask a health professional before use

Keep out of reach of children. In case of accidental ingestion, get medical help or contact a Poison Control Center right away

INDICATIONS AND USAGE

Directions Adults and children over 12 years

- Apply generously to affected area
- Massage into painful area until thoroughly absorbed into skin
- Repeat as necessary, but no more than 4 times daily
- Close cap tightly after use
- Keep carton as it contains important information
- Children 12 years or younger: Ask a doctor

INACTIVE INGREDIENT

Inactive ingredients DEA-cetyl phosphate, isopropyl myristate, methylparaben, polysorbate 60, propylparaben, purified lanolin, purified water, stearic acid, stearyl alcohol, trolamine

DOSAGE AND ADMINISTRATION

DISTRIBUTED BY: WALGREEN CO.

200 WILMOT RD., DEERFIELD, IL 60015

MADE IN KOREA

PACKAGE LABEL

Enter section text here